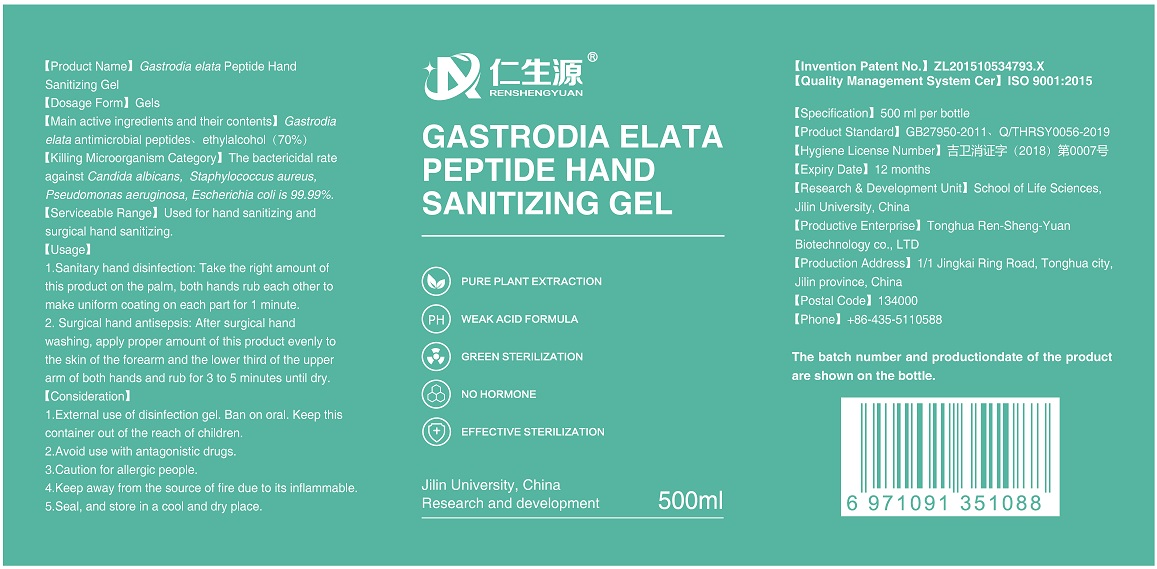 DRUG LABEL: Gastrodia elata Peptide Hand Sanitizing
NDC: 75449-1001 | Form: GEL
Manufacturer: Tonghua Ren-Sheng-Yuan Biotechnology Co., Ltd
Category: otc | Type: HUMAN OTC DRUG LABEL
Date: 20200424

ACTIVE INGREDIENTS: GASTRODIA ELATA WHOLE 27.5 g/500 mL; ALCOHOL 350 mL/500 mL
INACTIVE INGREDIENTS: GLYCERIN; WATER

RenShengYuan, 70% Ethanol, Hand Sanitizing, Gel, 500mL

Active Ingredient(s)

Alcohol 70% v/v. Purpose: Antiseptic.

Gastrodia elata Blume peptide 5.5% v/v. Purpose: bactericidal against Candida albicans, Staphylococcus aureus, Pseudomonas aeruginosa, Escherichia coli.

Purpose

Antiseptic, Hand Sanitizer

Use

Hand Sanitizer to help reduce bacteria that potentially can cause disease. For use when soap and water are not available.

Used for hand sanitizing and surgical hand sanitizing.

Warnings

1. External use of disinfection gel. Ban on oral. Keep this container out of the reach of children.
2. Avoid use with antagonistic drugs.
3. Caution for allergic people.
4. Keep away from the source of fire due to its inflammable.
5. Seal, and store in a cool and dry place.

Do not use

- on children less than 2 months of age
- on open skin wounds
- in the eyes. in case of contact, rinse eyes thoroughly with water

When using this product keep out of eyes, ears, and mouth.

In case of contact with eyes, rinse eyes thoroughly with water.

Stop use and ask a doctor if irritation and redness develop and persist for more than 72 hours.

Keep out of reach of children. If swallowed, get medical help or contact a Poison Control Center right away.

Directions

1.Sanitary hand disinfection: Take the right amount of this product on the palm, both hands rub each other to make uniform coating on each part for 1 minute.
2. Surgical hand antisepsis: After surgical hand washing, apply proper amount of this product evenly to the skin of the forearm and the lower third of the upper arm of both hands and rub for 3 to 5 minutes until dry.

Other information

Seal, and store in a cool and dry place.

Inactive ingredients

Water, Glycerine.